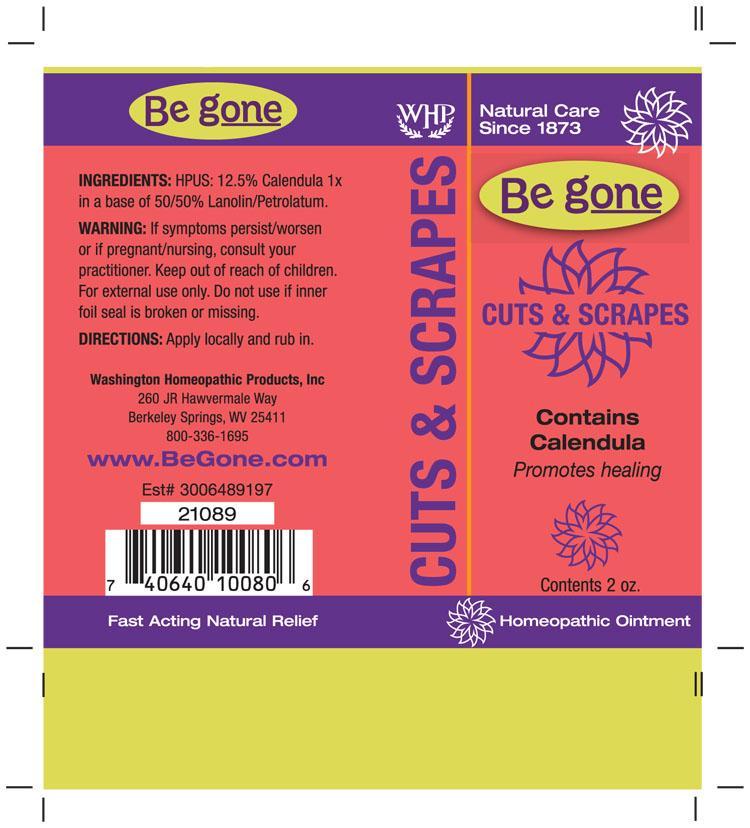 DRUG LABEL: Be gone Cuts and Scrapes
NDC: 68428-719 | Form: OINTMENT
Manufacturer: Washington Homeopathic Products
Category: homeopathic | Type: HUMAN OTC DRUG LABEL
Date: 20230330

ACTIVE INGREDIENTS: CALENDULA OFFICINALIS FLOWERING TOP 1 [hp_X]/56 g
INACTIVE INGREDIENTS: PETROLATUM; LANOLIN

Be Gone Cuts and Scrapes

ACTIVE INGREDIENTS

CALENDULA ø

USES

To relieve cuts, abrasions, dry/cracked skin, and sunburn.

KEEP OUT OF REACH OF CHILDREN

Keep this and all medicines out of reach of children.

INDICATIONS

CALENDULA Promotes healing

STOP USE AND ASK DOCTOR

For external use only. If symptoms persist/worsen or if pregnant/nursing, consult your practitioner.

DIRECTIONS

Apply locally and rub in.

INACTIVE INGREDIENTS

50% Lanolin

50% Petrolatum

PRINCIPAL DISPLAY PANEL

Be gone Cuts and Scrapes tube